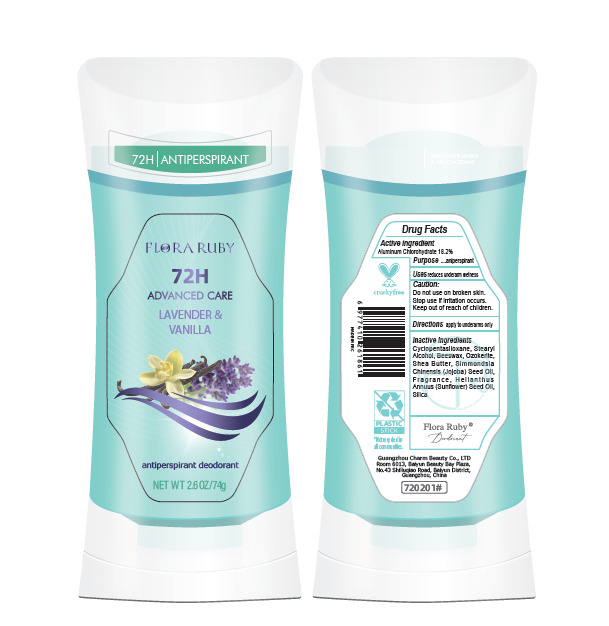 DRUG LABEL: ANTIPERSPIRANT DEODORANT
NDC: 85311-001 | Form: STICK
Manufacturer: Guangzhou Charm Beauty Trading Co., Ltd.
Category: otc | Type: HUMAN OTC DRUG LABEL
Date: 20250304

ACTIVE INGREDIENTS: ALUMINUM CHLOROHYDRATE 18.2 g/100 g
INACTIVE INGREDIENTS: HELIANTHUS ANNUUS FLOWERING TOP; CLOVE; CYCLOPENTASILOXANE; STEARYL ALCOHOL; BEESWAX; CERESIN; BUTYROSPERMUM PARKII (SHEA) BUTTER; SIMMONDSIA CHINENSIS (JOJOBA) SEED OIL; SILICA

85311-001
ANTIPERSPIRANT DEODORANT

Active Ingredient(s)

ALUMINUM CHLOROHYDRATE 18.2%

Purpose

aniperspirant

Use

Uses reduces underarm wetness

Warnings

Do not use on broken skin.
Stop use if irritation occurs.
Keep out of reach of children.

Do not use on broken skin.

When using this product keep out of eyes, ears, and mouth.

Stop use if irritation occurs.

Keep out of reach of children.

Directions

Directions apply to underarms only

Other information

No Data

Inactive ingredients

Cyclopentasiloxane, Stearyl Alcohol, Beeswax, Ozokerite, Shea Butter, Simmondsia
Chinensis (Jojoba) Seed Oil, Fragrance, Helianthus Annuus (Sunflower) Seed Oil,
Silica